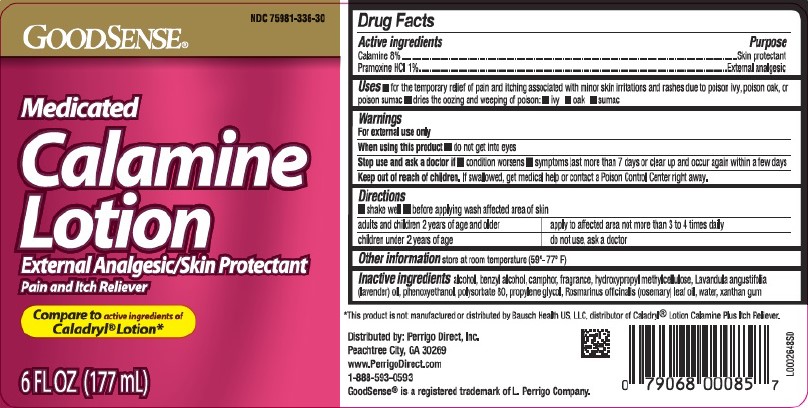 DRUG LABEL: Calamine
NDC: 75981-336 | Form: LOTION
Manufacturer: Perrigo Direct, Inc
Category: otc | Type: HUMAN OTC DRUG LABEL
Date: 20260219

ACTIVE INGREDIENTS: FERRIC OXIDE RED 80 mg/1 mL; PRAMOXINE HYDROCHLORIDE 10 mg/1 mL
INACTIVE INGREDIENTS: ALCOHOL; BENZYL ALCOHOL; CAMPHOR (SYNTHETIC); HYPROMELLOSE, UNSPECIFIED; LAVENDER OIL; PHENOXYETHANOL; POLYSORBATE 80; PROPYLENE GLYCOL; ROSEMARY OIL; WATER; XANTHAN GUM

Good Sense 336.003/336AG
Medicated Calamine Lotion

Active ingredients

Calamine 8%

Pramoxine HCl 1%

Purpose

Skin protectant

External analgesic

Uses

- for the temporary relief of pain and itching associated with minor skin irritations and rashes due to poison ivy, poison oak, or poison sumac
- dries the oozing and weeping of poison: -ivy -oak -sumac

Warnings

For external use only

When using this product

- do not get into eyes

Stop use and ask a doctor if

- condition worsens
- symptoms last more than 7 days or clear up and occur again within a few days

Keep out of reach of children.

If swallowed, get medical help or contact a Poison Control Center right away.

Directions

- shake well
- before applying wash affected area of skin

Adults and children 2 years of age and older - apply to affected area not more than 3 to 4 times daily

Children under 2 years of age - do not use, ask a doctor

Other information

store at room temperature (59°-77°F)

Inactive ingredients

alcohol, benzyl alcohol, camphor, fragrance, hydroxypropyl methylcellulose, Lavandula angustifolia (lavender) oil, phenoxyethanol, polysorbate 80, propylene glycol, Rosmarinus officinalis (rosemary) leaf oil, water, xanthan gum

Disclaimer

*This product is not manufactured or distributed by Bausch Health US, LLC, distributor of CaladrylLotion Calamine Plus Itch Reliever.

Adverse reaction

Distributed by Perrigo Direct, Inc.

Peachtree City, GA 30269

www.PerrigoDirect.com

1-888-593-0593

Good Sense®is a registered trademark of L. Perrigo Company.

Principal display panel

NDC 75981-336-30

GoodSense®

Medicated Calamine Lotion

External Analgesic/Skin Protectant

Pain and Itch Reliever

Compare to active ingredients of Caladryl®Lotion*

6 FL OZ (177 mL)